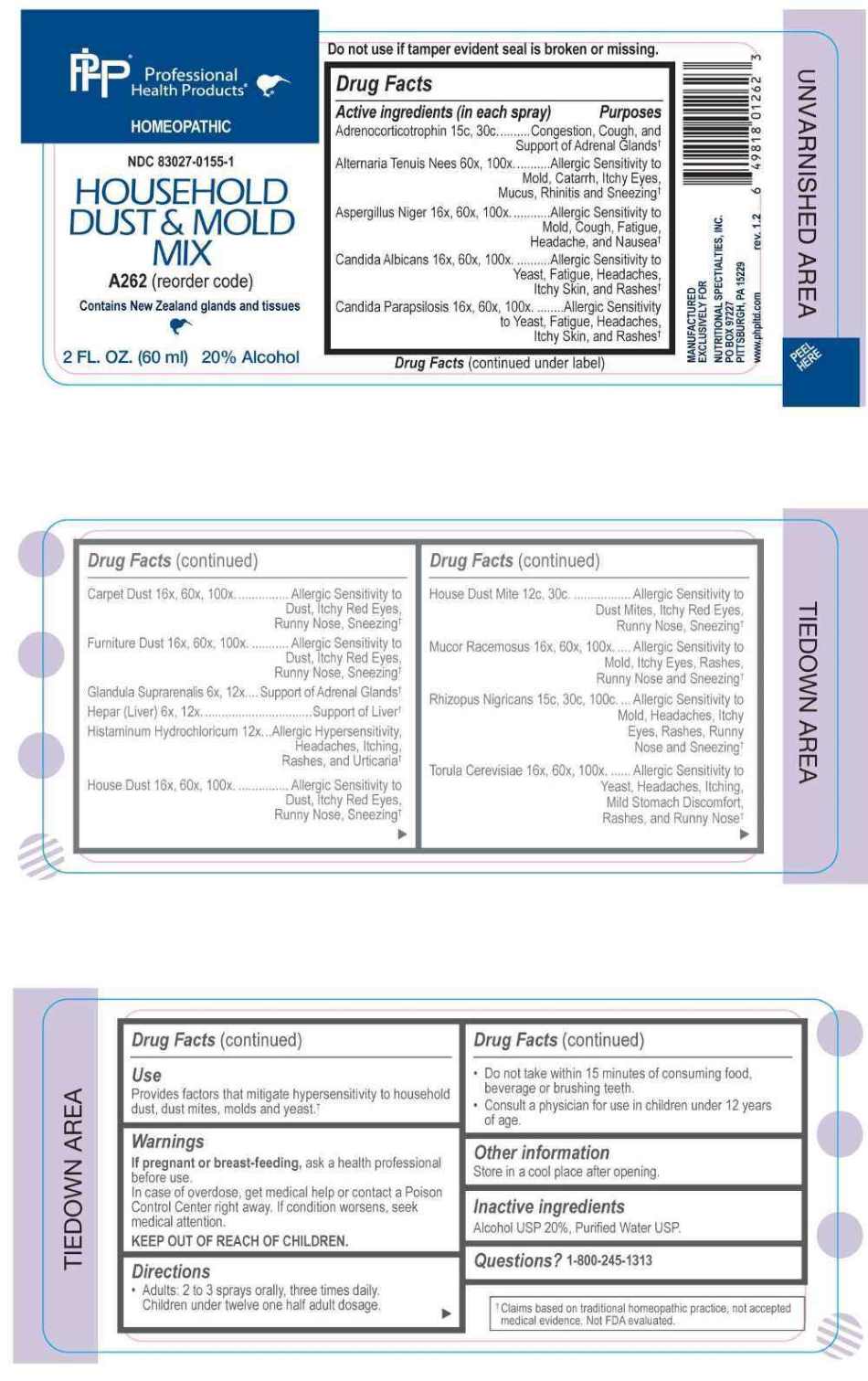 DRUG LABEL: Household Dust and Mold Mix
NDC: 83027-0155 | Form: SPRAY
Manufacturer: Nutritional Specialties, Inc.
Category: homeopathic | Type: HUMAN OTC DRUG LABEL
Date: 20251002

ACTIVE INGREDIENTS: BOS TAURUS ADRENAL GLAND 6 [hp_X]/1 mL; HEPARIN, BOVINE 6 [hp_X]/1 mL; HISTAMINE DIHYDROCHLORIDE 12 [hp_X]/1 mL; ALTERNARIA ALTERNATA 60 [hp_X]/1 mL; ASPERGILLUS NIGER VAR. NIGER 16 [hp_X]/1 mL; CANDIDA ALBICANS 16 [hp_X]/1 mL; CANDIDA PARAPSILOSIS 16 [hp_X]/1 mL; HOUSE DUST 16 [hp_X]/1 mL; MUCOR RACEMOSUS 16 [hp_X]/1 mL; SACCHAROMYCES CEREVISIAE 16 [hp_X]/1 mL; DERMATOPHAGOIDES PTERONYSSINUS 12 [hp_C]/1 mL; CORTICOTROPIN 15 [hp_C]/1 mL; RHIZOPUS STOLONIFER 15 [hp_C]/1 mL
INACTIVE INGREDIENTS: WATER; ALCOHOL

DRUG FACTS:

ACTIVE INGREDIENTS:

Adrenocorticotrophin 15C, 30C, Alternaria Tenuis Nees 60X, 100X, Aspergillus Niger 16X, 60X, 100X, Candida Albicans 16X, 60X, 100X, Candida Parapsilosis 16X, 60X, 100X, Carpet Dust 16X, 60X, 100X, Furniture Dust 16X, 60X, 100X, Glandula Suprarenalis 6X, 12X, Hepar (Liver) 6X, 12X, Histaminum Hydrochloricum 12X, House Dust 16X, 60X, 100X, House Dust Mite 12C, 30C, Mucor Racemosus 16X, 60X, 100X, Rhizopus Nigricans 15C, 30C, 100C, Torula Cerevisiae 16X, 60X, 100X.

PURPOSE:

Adrenocorticotrophin – Congestion, Cough, and Support of Adrenal Glands,† Alternaria Tenuis Nees – Allergic Sensitivity to Mold, Catarrh, Itchy Eyes, Mucus, Rhinitis and Sneezing,† Aspergillus Niger – Allergic Sensitivity to Mold, Cough, Fatigue, Headache, and Nausea,† Candida Albicans – Allergic Sensitivity to Yeast, Fatigue, Headaches, Itchy Skin, and Rashes,† Candida Parapsilosis – Allergic Sensitivity to Yeast, Fatigue, Headaches, Itchy Skin, and Rashes,† Carpet Dust – Allergic Sensitivity to Dust, Itchy Red Eyes, Runny Nose, Sneezing,† Furniture Dust - Allergic Sensitivity to Dust, Itchy Red Eyes, Runny Nose, Sneezing,† Glandula Suprarenalis -Support of Adrenal Glands,† Hepar (Liver) – Support of Liver,† Histaminum Hydrochloricum – Allergic Hypersensitivity, Headaches, Itching, Rashes, and Urticaria,† House Dust - Allergic Sensitivity to Dust, Itchy Red Eyes, Runny Nose, Sneezing,† House Dust Mite - Allergic Sensitivity to Dust Mites, Itchy Red Eyes, Runny Nose, Sneezing,† Mucor Racemosus – Allergic Sensitivity to Mold, Itchy Eyes, rashes, Runny Nose, and Sneezing,† Rhizopus Nigricans – Allergic Sensitivity to Mold, Headaches, Itchy Eyes, Rashes, Runny Nose and Sneezing,† Torula Cerevisiae – Allergic Sensitivity to Yeast, Headaches, Itching, Mild Stomach Discomfort, Rashes, and Runny Nose†

†Claims based on traditional homeopathic practice, not accepted medical evidence. Not FDA evaluated.

USES:

Provides factors that mitigate hypersensitivity to household dust, dust mites, molds and yeast.†

†Claims based on traditional homeopathic practice, not accepted medical evidence. Not FDA evaluated.

WARNINGS:

If pregnant or breast-feeding, ask a health professional before use.

In case of overdose, get medical help or contact a Poison Control Center right away.

If condition worsens, seek medical attention.

KEEP OUT OF REACH OF CHILDREN

Do not use if tamper evident seal is broken or missing.

Store in a cool place after opening

KEEP OUT OF REACH OF CHILDREN:

In case of overdose, get medical help or contact a Poison Control Center right away.

DIRECTIONS:

• Adults: 2 to 3 sprays orally, three times daily. Children under twelve one half adult dosage.

• Do not take within 15 minutes of consuming food, beverage or brushing teeth.

• Consult a physician for use in children under 12 years of age.

INACTIVE INGREDIENTS:

Alcohol USP 20%, Purified Water USP.

QUESTIONS:

MANUFACTURED EXCLUSIVELY FOR

NUTRITIONAL SPECIALTIES, INC.

PO BOX 97227

PITTSBURGH, PA 15229

www.phpitd.com

1-800-245-1313

PACKAGE LABEL DISPLAY:

Professional Health Products

HOMEOPATHIC

NDC 83027-0155-1

HOUSEHOLD DUST & MOLD MIX

2 FL. OZ. (60 ml)